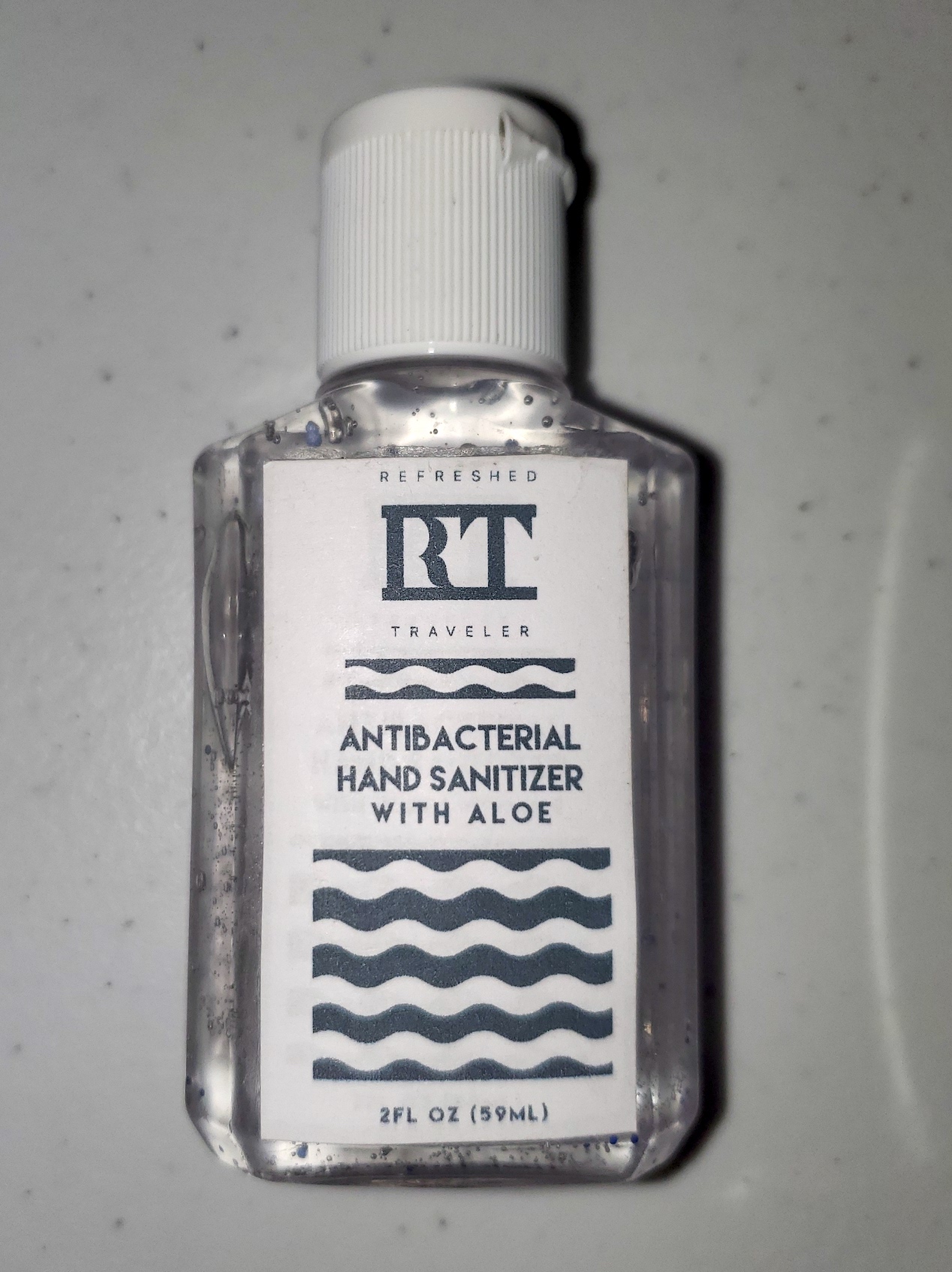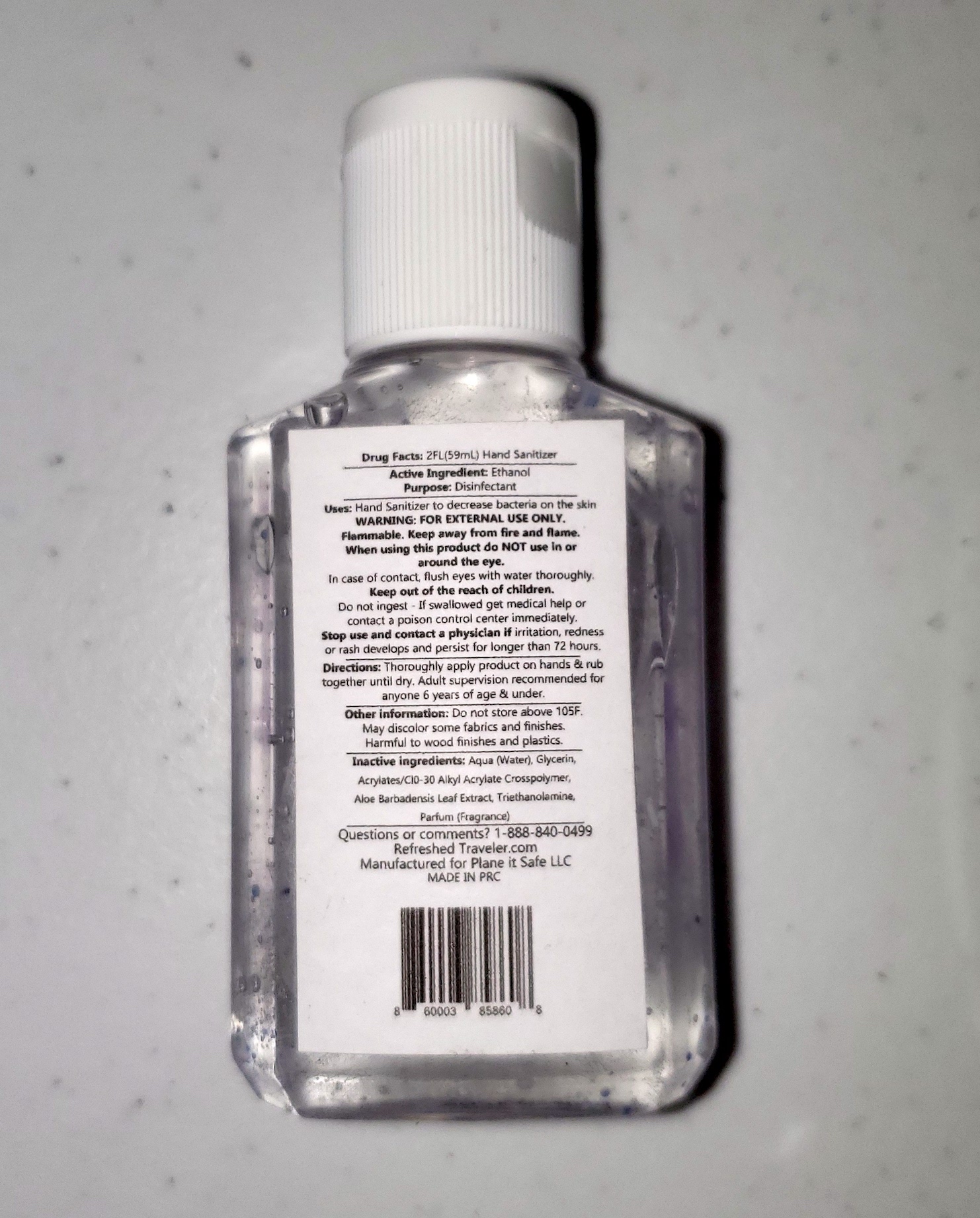 DRUG LABEL: Refreshed Traveler Hand Sanitizer with Aloe
NDC: 72920-2013 | Form: GEL
Manufacturer: Plane It Safe LLC
Category: otc | Type: HUMAN OTC DRUG LABEL
Date: 20211224

ACTIVE INGREDIENTS: ALCOHOL 70 mL/100 mL
INACTIVE INGREDIENTS: WATER

Refreshed Traveler Hand Sanitizer with Aloe

Warning:

For External Use Only

ACTIVE INGREDIENT

Ethanol 70%

Stop use and contact a physician if redness or rash develops or persists longer than 72 hours.

PURPOSE

To decrease bacteria on hands

INDICATIONS AND USAGE

Antiseptic to reduce bacteria on the hands

Directions

Apply on hands and rub together until dry

INACTIVE INGREDIENT

(Aqua) Water, Glycerin, Acrylates/C10-30 Alkyl Acrylate Crosspolymer, Aloe Barbadensis Leaf Extract, Triethanolamine, Parfun (Fragrance)

USE:

Hand Sanitizer to decrease bacteria on the hands